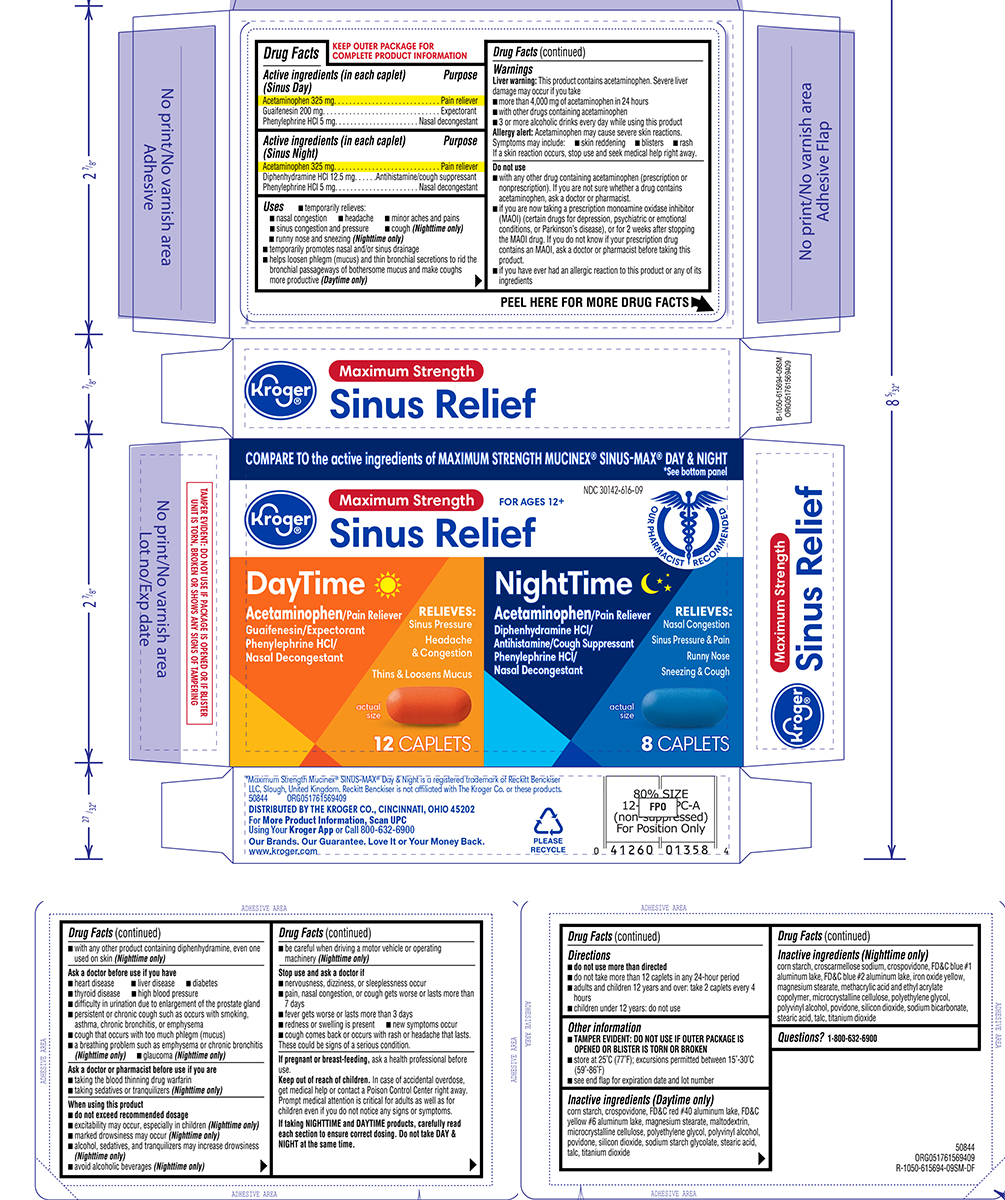 DRUG LABEL: Sinus Relief
NDC: 30142-616 | Form: KIT | Route: ORAL
Manufacturer: Kroger Company
Category: otc | Type: HUMAN OTC DRUG LABEL
Date: 20250719

ACTIVE INGREDIENTS: ACETAMINOPHEN 325 mg/1 1; GUAIFENESIN 200 mg/1 1; PHENYLEPHRINE HYDROCHLORIDE 5 mg/1 1; ACETAMINOPHEN 325 mg/1 1; DIPHENHYDRAMINE HYDROCHLORIDE 12.5 mg/1 1; PHENYLEPHRINE HYDROCHLORIDE 5 mg/1 1
INACTIVE INGREDIENTS: STARCH, CORN; CROSPOVIDONE; FD&C RED NO. 40; FD&C YELLOW NO. 6; MAGNESIUM STEARATE; MALTODEXTRIN; MICROCRYSTALLINE CELLULOSE; POLYETHYLENE GLYCOL, UNSPECIFIED; POLYVINYL ALCOHOL, UNSPECIFIED; POVIDONE, UNSPECIFIED; SILICON DIOXIDE; SODIUM STARCH GLYCOLATE TYPE A POTATO; STEARIC ACID; TALC; TITANIUM DIOXIDE; STARCH, CORN; CROSCARMELLOSE SODIUM; CROSPOVIDONE; FD&C BLUE NO. 1 ALUMINUM LAKE; FD&C BLUE NO. 2--ALUMINUM LAKE; FERRIC OXIDE YELLOW; MAGNESIUM STEARATE; METHACRYLIC ACID AND ETHYL ACRYLATE COPOLYMER; MICROCRYSTALLINE CELLULOSE; POLYETHYLENE GLYCOL, UNSPECIFIED; POLYVINYL ALCOHOL, UNSPECIFIED; POVIDONE, UNSPECIFIED; SILICON DIOXIDE; SODIUM BICARBONATE; STEARIC ACID; TALC; TITANIUM DIOXIDE

Kroger 44-615694

Active ingredients (in each caplet) (Sinus Day)

Acetaminophen 325 mg
Guaifenesin 200 mg
Phenylephrine HCl 5 mg

Purpose

Pain reliever
Expectorant
Nasal decongestant

Active ingredients (in each caplet) (Sinus Night)

Acetaminophen 325 mg
Diphenhydramine HCl 12.5 mg
Phenylephrine HCl 5 mg

Purpose

Pain reliever
Antihistamine/cough suppressant
Nasal decongestant

Uses

- temporarily relieves:
  - nasal congestion
  - headache
  - minor aches and pains
  - sinus congestion and pressure
  - cough (Nighttime only)
  - runny nose and sneezing (Nighttime only)
- temporarily promotes nasal and/or sinus drainage
- helps loosen phlegm (mucus) and thin bronchial secretions to rid the bronchial passageways of bothersome mucus and make coughs more productive (Daytime only)

Warnings

Liver warning: This product contains acetaminophen. Severe liver damage may occur if you take

- more than 4,000 mg of acetaminophen in 24 hours
- with other drugs containing acetaminophen
- 3 or more alcoholic drinks every day while using this product

Allergy alert: Acetaminophen may cause severe skin reactions. Symptoms may include:

- skin reddening
- blisters
- rash

If a skin reaction occurs, stop use and seek medical help right away.

Do not use

- with any other drug containing acetaminophen (prescription or nonprescription). If you are not sure whether a drug contains acetaminophen, ask a doctor or pharmacist.
- if you are now taking a prescription monoamine oxidase inhibitor (MAOI) (certain drugs for depression, psychiatric or emotional conditions, or Parkinson’s disease), or for 2 weeks after stopping the MAOI drug. If you do not know if your prescription drug contains an MAOI, ask a doctor or pharmacist before taking this product.
- if you have ever had an allergic reaction to this product or any of its ingredients
- with any other product containing diphenhydramine, even one used on skin (Nighttime only)

Ask a doctor before use if you have

- heart disease
- high blood pressure
- liver disease
- thyroid disease
- diabetes
- difficulty in urination due to enlargement of the prostate gland
- persistent or chronic cough such as occurs with smoking, asthma, chronic bronchitis, or emphysema
- cough that occurs with too much phlegm (mucus)
- a breathing problem such as emphysema or chronic bronchitis (Nighttime only)
- glaucoma (Nighttime only)

Ask a doctor or pharmacist before use if you are

- taking the blood thinning drug warfarin
- taking sedatives or tranquilizers (Nighttime only)

When using this product

- do not exceed recommended dosage
- excitability may occur, especially in children (Nighttime only)
- marked drowsiness may occur (Nighttime only)
- alcohol, sedatives, and tranquilizers may increase drowsiness (Nighttime only)
- be careful when driving a motor vehicle or operating machinery (Nighttime only)
- avoid alcoholic beverages (Nighttime only)

Stop use and ask a doctor if

- nervousness, dizziness, or sleeplessness occur
- pain, nasal congestion, or cough gets worse or lasts more than 7 days
- new symptoms occur
- fever gets worse or lasts more than 3 days
- redness or swelling is present
- cough comes back or occurs with rash or headache that lasts.

These could be signs of a serious condition.

If pregnant or breast-feeding,

ask a health professional before use.

Keep out of reach of children.

In case of accidental overdose, get medical help or contact a Poison Control Center (1-800-222-1222) right away. Prompt medical attention is critical for adults as well as for children even if you do not notice any signs or symptoms.

If taking NIGHTTIME and DAYTIME products, carefully read each section to ensure correct dosing. Do not take DAY & NIGHT at the same time.

Directions

- do not use more than directed
- do not take more than 12 caplets in any 24-hour period
- adults and children 12 years and over: take 2 caplets every 4 hours
- children under 12 years: do not use

Other information

- TAMPER EVIDENT: DO NOT USE IF OUTER PACKAGE IS OPENED OR BLISTER IS TORN OR BROKEN
- store at 25°C (77°F); excursions permitted between 15°-30°C (59°-86°F)
- see end flap for expiration date and lot number

Inactive ingredients (Daytime only)

corn starch, crospovidone, FD&C red #40 aluminum lake, FD&C yellow #6 aluminum lake, magnesium stearate, maltodextrin, microcrystalline cellulose, polyethylene glycol, polyvinyl alcohol, povidone, silicon dioxide, sodium starch glycolate, stearic acid, talc, titanium dioxide

Inactive ingredients (Nighttime only)

corn starch, croscarmellose sodium, crospovidone, FD&C blue #1 aluminum lake, FD&C blue #2 aluminum lake, iron oxide yellow, magnesium stearate, methacrylic acid and ethyl acrylate copolymer, microcrystalline cellulose, polyethylene glycol, polyvinyl alcohol, povidone, silicon dioxide, sodium bicarbonate, stearic acid, talc, titanium dioxide

Questions or comments?

1-800-426-9391

Principal display panel

COMPARE TO the active ingredients of MAXIMUM STRENGTH MUCINEX® SINUSMAX® DAY & NIGHT

*See bottom panel

NDC 30142-616-09

OUR PHARMACIST RECCOMMENDED

Maximum Strength

FOR AGES 12+

Kroger®

Sinus Relief

DAYTIME

Acetaminophen/ Pain Reliever
Guafenesin / Expectorant
Phenylephrine HCl/ Nasal Decongestant

RELIEVES:

Sinus Pressure

Headache

& Congestion

Thins & Loosens Mucus

actual size

12 CAPLETS

NIGHTTIME
Acetaminophen/Pain Reliever
Diphenhydramine HCl/
Antihistamine/Cough Suppressant
Phenylephrine HCl/
Nasal Decongestant

RELIEVES:

Nasal Congestion

Sinus Pressure & Pain

Runny Nose

Sneezing & Cough

actual size

8 CAPLETS

*Maximum Strength Mucinex® SINUS-MAX® Day & Night is a registered trademark of Reckitt Benckiser LLC, Slough, United Kingdom. Reckitt Benckiser is not aliated with The Kroger Co. or these products.

50844 ORG051761569409

DISTRIBUTED BY THE KROGER CO., CINCINNATI, OHIO 45202
For More Product Information, Scan UPC
Using Your Kroger App or Call 800-632-6900
Our Brands. Our Guarantee. Love It or Your Money Back.
www.kroger.com

PLEASE RECYCLE

TAMPER EVIDENT: DO NOT USE IF PACKAGE IS OPENED OR IF BLISTER

UNIT IS TORN, BROKEN OR SHOWS ANY SIGNS OF TAMPERING

44-615694